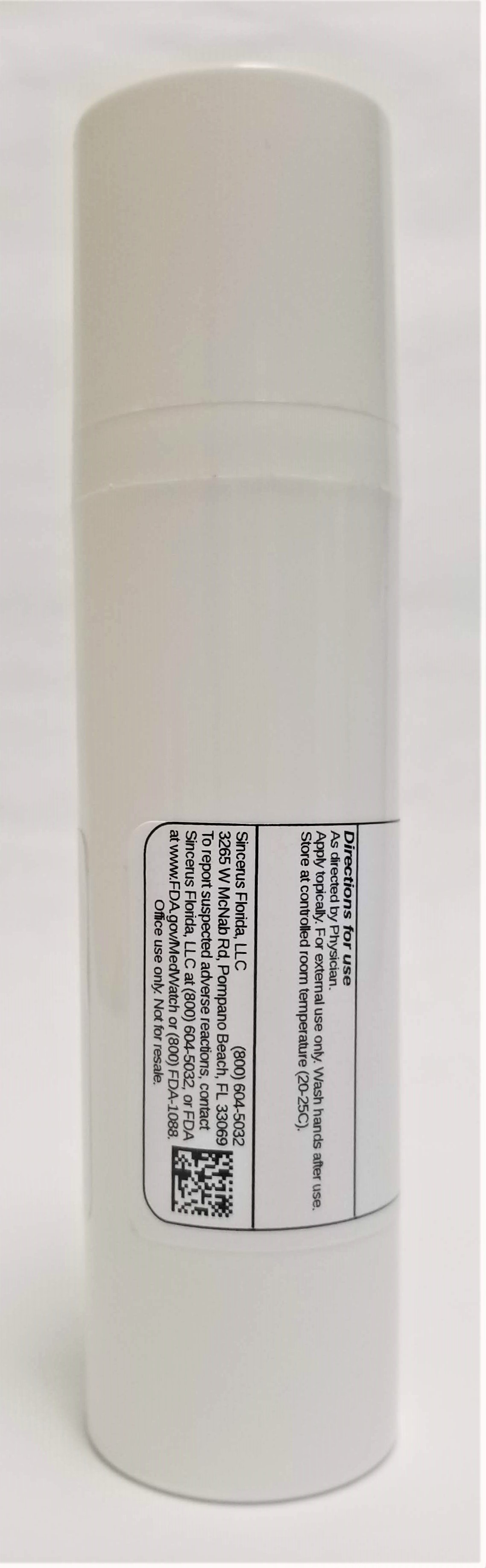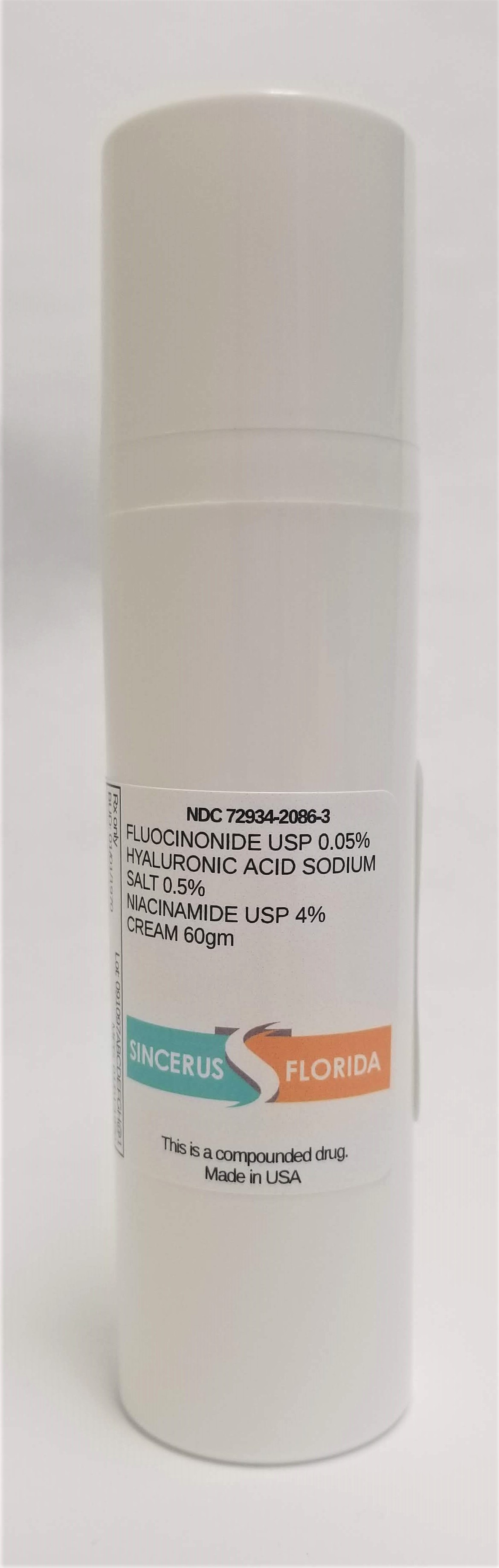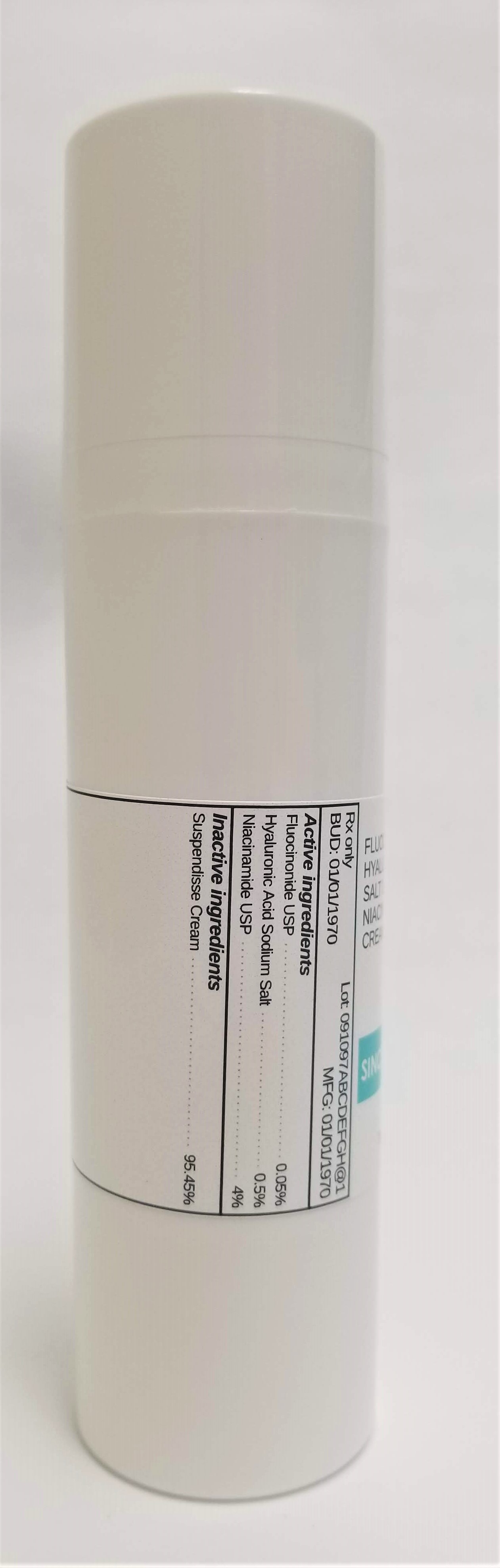 DRUG LABEL: FLUOCINONIDE 0.05% / HYALURONIC ACID SODIUM SALT 0.5% / NIACINAMIDE 4%
NDC: 72934-2086 | Form: CREAM
Manufacturer: Sincerus Florida, LLC
Category: prescription | Type: HUMAN PRESCRIPTION DRUG LABEL
Date: 20190522

ACTIVE INGREDIENTS: FLUOCINONIDE 0.05 g/100 g; HYALURONATE SODIUM 0.5 g/100 g

FLUOCINONIDE 0.05% / HYALURONIC ACID SODIUM SALT 0.5% / NIACINAMIDE 4%